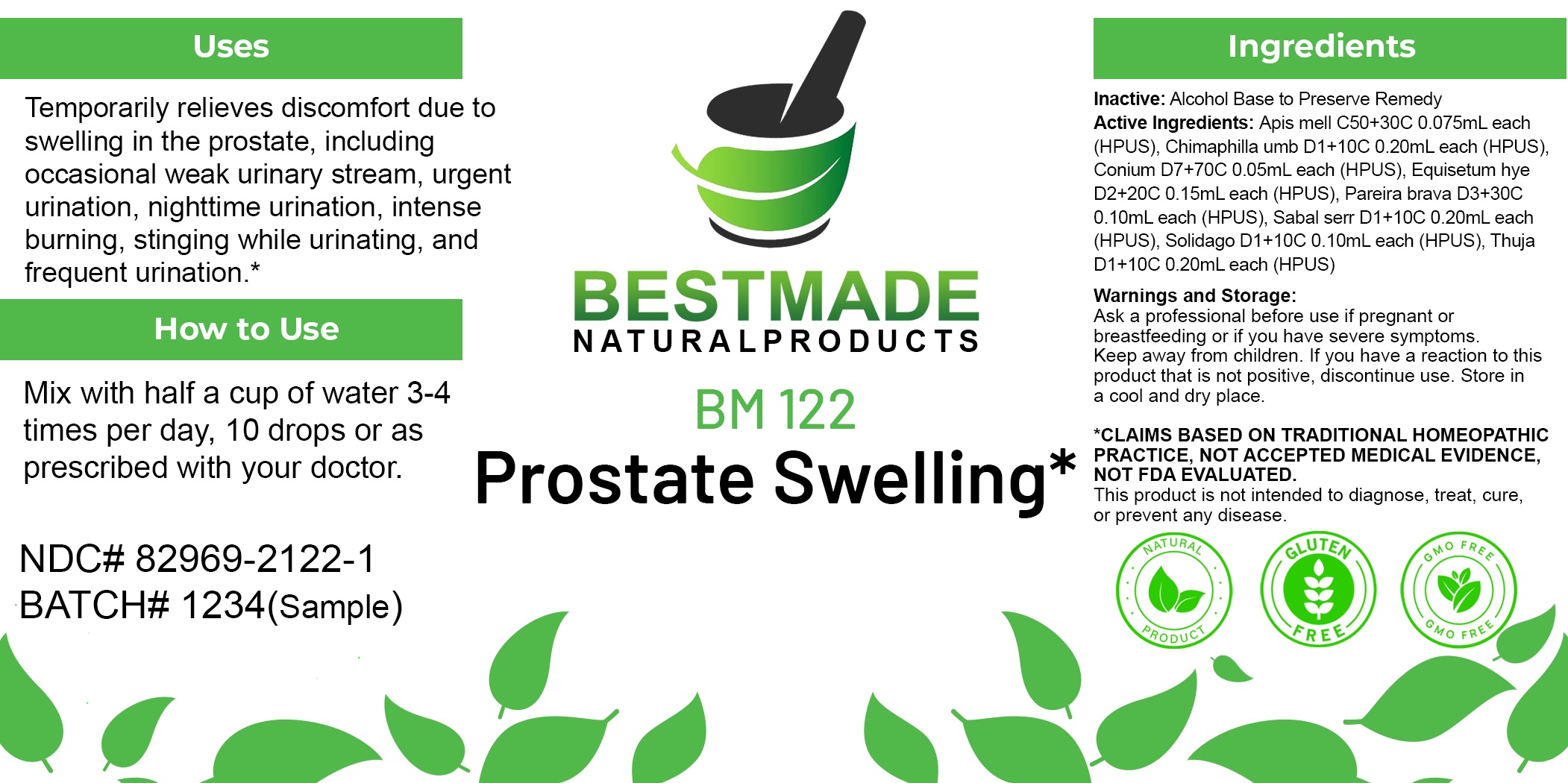 DRUG LABEL: Bestmade Natural Products BM122
NDC: 82969-2122 | Form: LIQUID
Manufacturer: Bestmade Natural Products
Category: homeopathic | Type: HUMAN OTC DRUG LABEL
Date: 20250207

ACTIVE INGREDIENTS: CHIMAPHILA UMBELLATA WHOLE 30 [hp_C]/30 [hp_C]; CHONDRODENDRON TOMENTOSUM ROOT 30 [hp_C]/30 [hp_C]; CONIUM MACULATUM FLOWERING TOP 30 [hp_C]/30 [hp_C]; APIS MELLIFERA 30 [hp_C]/30 [hp_C]; SAW PALMETTO 30 [hp_C]/30 [hp_C]; THUJA OCCIDENTALIS LEAFY TWIG 30 [hp_C]/30 [hp_C]; SOLIDAGO VIRGAUREA FLOWERING TOP 30 [hp_C]/30 [hp_C]; EQUISETUM HYEMALE WHOLE 30 [hp_C]/30 [hp_C]
INACTIVE INGREDIENTS: ALCOHOL 30 [hp_C]/30 [hp_C]

BM122

DOSAGE AND ADMINISTRATION

How to Use

Mix with half a cup of water 3-4 times per day. Ages 12 or older, 10 drops. Ages 12-2, 5 drops. Ages 2 and under, consult your Doctor.

Inactive:

Alcohol Base to Preserve Product

ACTIVE INGREDIENTS:

Apis mell C50+30C 0.075mL each (HPUS), Chimaphilla umb D1+10C 0.20mL each (HPUS), Conium D7+70C 0.05mL each (HPUS), Equisetum hye D2+20C 0.15mL each (HPUS), Pareira brava D3+30C 0.10mL each (HPUS), Sabal serr D1+10C 0.20mL each (HPUS), Solidago D1+10C 0.10mL each (HPUS), Thuja D1+10C 0.20mL each (HPUS)

Uses
Temporarily relieves discomfort due to swelling in the prostate, including occasional weak urinary stream, urgent urination, nighttime urination, intense burning, stinging while urinating, and frequent urination.*

Uses
Temporarily relieves discomfort due to swelling in the prostate, including occasional weak urinary stream, urgent urination, nighttime urination, intense burning, stinging while urinating, and frequent urination.*

KEEP OUT OF REACH OF CHILDREN

Warnings and Storage:

Ask a professional before use if pregnant or breastfeeding or if you have severe symptoms.

Keep away from children. If you have a reaction to this product that is not positive, discontinue use. Store in a cool and dry place

*CLAIMS BASED ON TRADITIONAL HOMEOPATHIC PRACTICE, NOT ACCEPTED MEDICAL EVIDENCE NOT FDA EVALUATED.
This product is not intended to diagnose, treat, cure, or prevent any disease.

Warnings and Storage:

Ask a professional before use if pregnant or breastfeeding or if you have severe symptoms.

Keep away from children. If you have a reaction to this product that is not positive, discontinue use. Store in a cool and dry place

*CLAIMS BASED ON TRADITIONAL HOMEOPATHIC PRACTICE, NOT ACCEPTED MEDICAL EVIDENCE NOT FDA EVALUATED.
This product is not intended to diagnose, treat, cure, or prevent any disease.

Entire package label